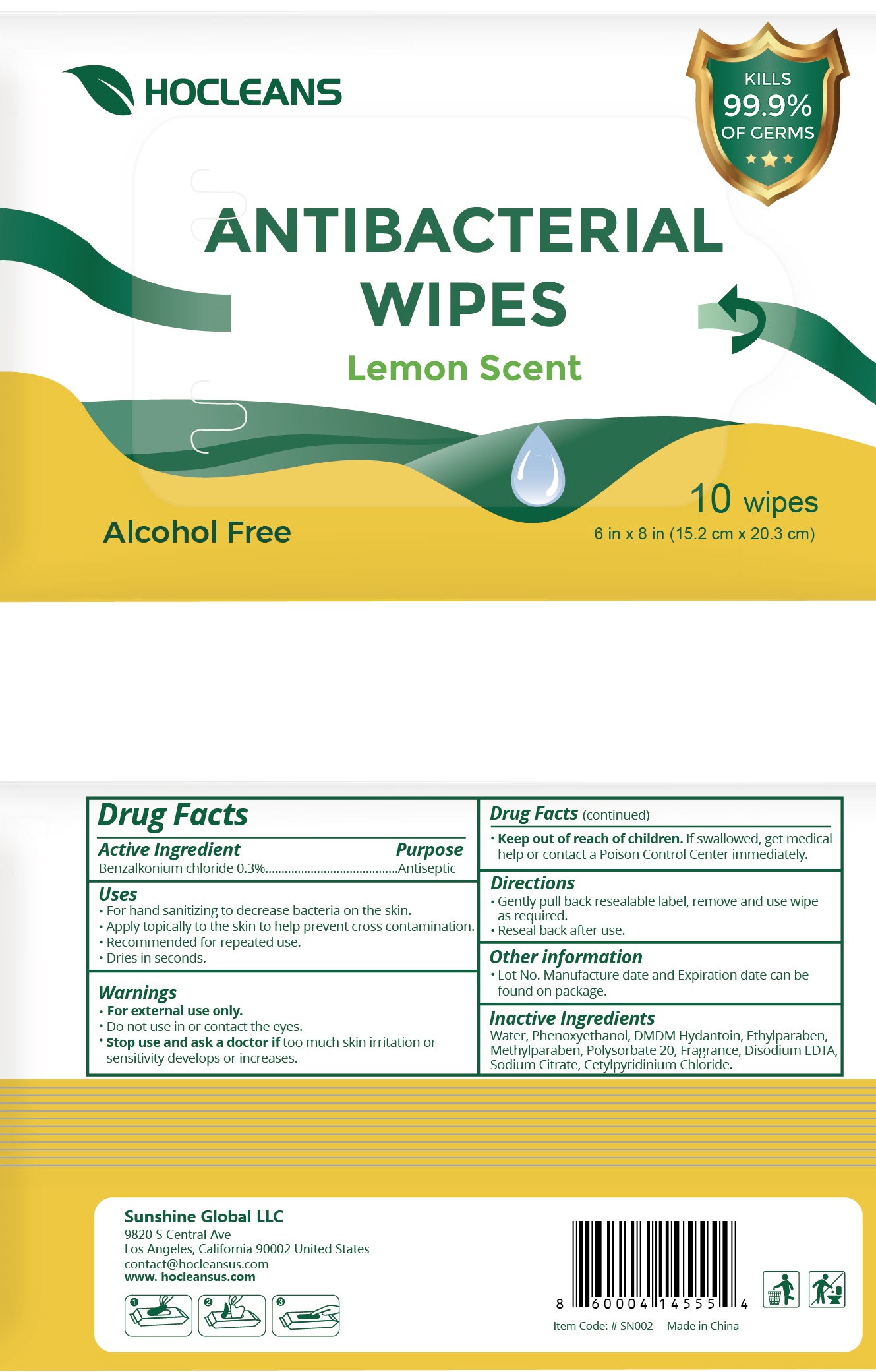 DRUG LABEL: Antibacterial wipes Lemon Scent
NDC: 77907-014 | Form: SWAB
Manufacturer: Hangzhou Yitong Biotech Co., Ltd.
Category: otc | Type: HUMAN OTC DRUG LABEL
Date: 20200629

ACTIVE INGREDIENTS: BENZALKONIUM CHLORIDE 0.30 g/100 g
INACTIVE INGREDIENTS: water; DMDM HYDANTOIN; ETHYLPARABEN; PHENOXYETHANOL; METHYLPARABEN; POLYSORBATE 20; SODIUM CITRATE; CETYLPYRIDINIUM CHLORIDE

Antibacterial Wipes

Active Ingredient

Benzalkonium Chloride 0.3%

Purpose

Antiseptic

USE

- For hand sanitizing to decrease bacteria on the skin.
- Apply topically to the skin to hlep prevent cross contamination.
- Recommended for repeated use.
- Dries in seconds.

Warning

- For external use only.
- Do not use in or contact the eyes

- Stop use and ask a doctor, if too much skin irritaion and sensitivity develops or increases.

KEEP OUT OF REACH OF CHILDREN

If swallowed, get medical help or contact a Poison Contrl Center immediately.

Directions

- Gently pull back resealable label, remove and use wipe as required.
- Reseal back after use.

Inactive ingredients

Water, Phenoxyethanol, DMDM Hydantoin, Ethylparaben, Methylparaben, Polysorbate 20, Fragrance, Disodium EDTA, Sodium Citrate, Cetylpyridinium Chloride.